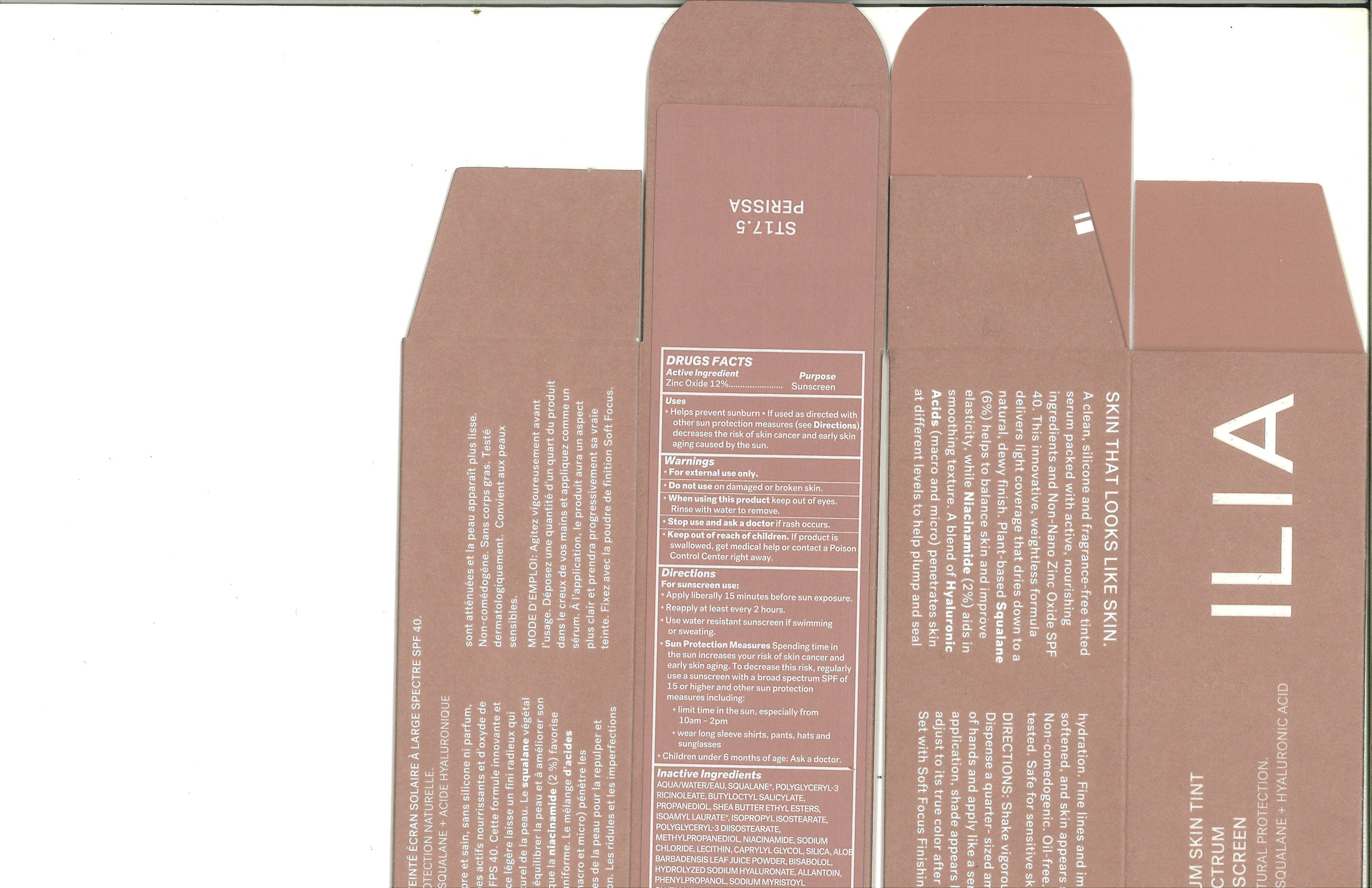 DRUG LABEL: ILIA SUPER SERUM SKIN TINT (ST17.5 PERISSA)
NDC: 81110-059 | Form: LOTION
Manufacturer: Ilia, Inc.
Category: otc | Type: HUMAN OTC DRUG LABEL
Date: 20251030

ACTIVE INGREDIENTS: ZINC OXIDE 132 mg/1 mL
INACTIVE INGREDIENTS: ALOE VERA LEAF; LECITHIN, SOYBEAN; ALLANTOIN; SILICON DIOXIDE; SQUALANE; CAPRYLYL GLYCOL; BUTYLOCTYL SALICYLATE; HYALURONATE SODIUM; TITANIUM DIOXIDE; SODIUM MYRISTOYL GLUTAMATE; ALUMINUM HYDROXIDE; WATER; NIACINAMIDE; PROPANEDIOL; SODIUM CHLORIDE; PHENYLPROPANOL; METHYLPROPANEDIOL; SHEA BUTTER; ISOAMYL LAURATE; POLYGLYCERYL-3 DIISOSTEARATE; ISOPROPYL ISOSTEARATE; .ALPHA.-BISABOLOL, (+)-

ILIA SUPER SERUM SKIN TINT (ST17.5 PERISSA)